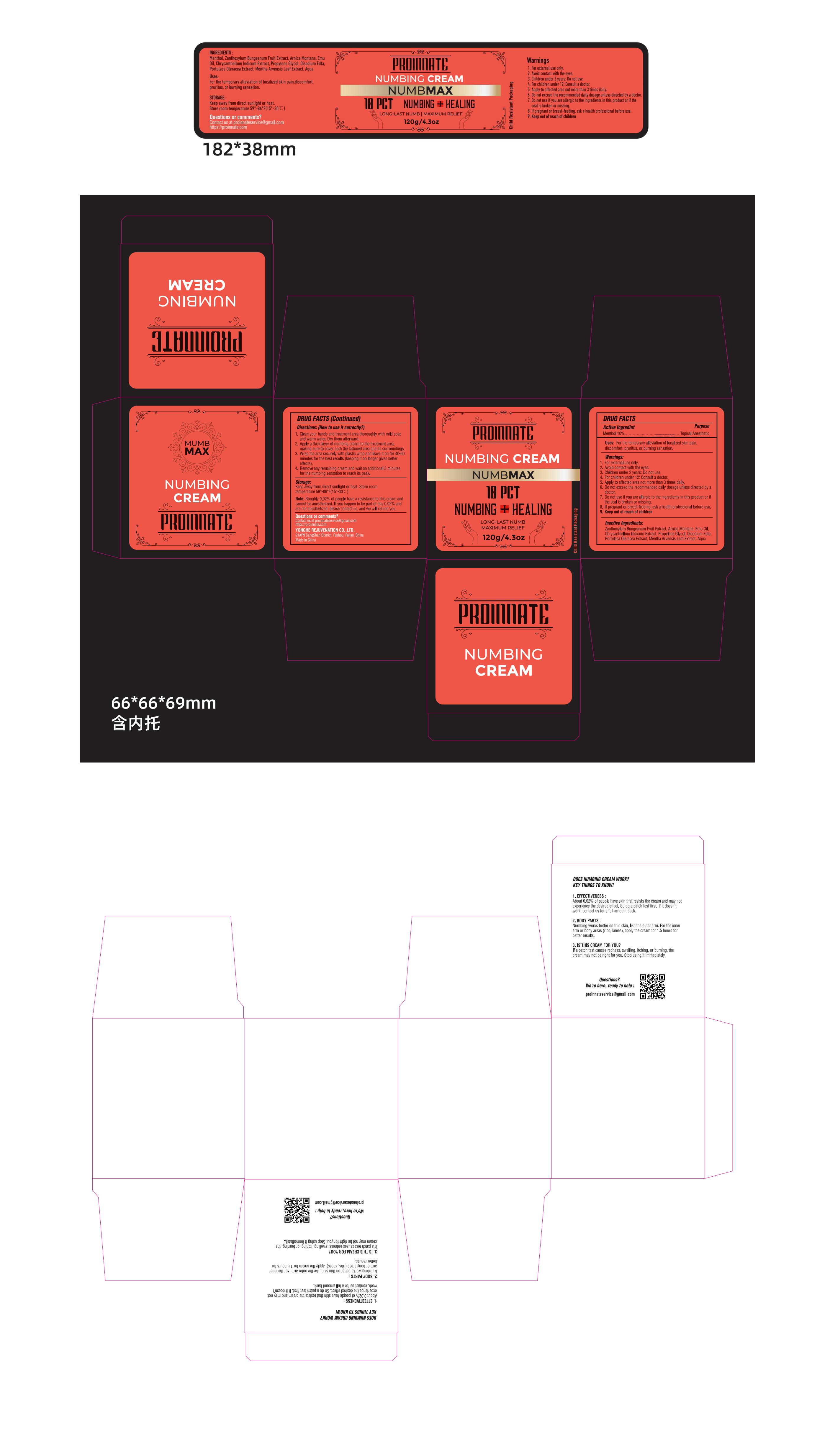 DRUG LABEL: PROINNATE Numbing Cream
NDC: 60771-0024 | Form: CREAM
Manufacturer: Guangzhou Haishi Biological Technology Co., Ltd.
Category: otc | Type: HUMAN OTC DRUG LABEL
Date: 20250716

ACTIVE INGREDIENTS: MENTHOL 10 g/100 g
INACTIVE INGREDIENTS: ARNICA MONTANA; EMU OIL

PROINNATE NUMBING CREAM

Active ingredients

Menthol 10%

Purpose

For the temporary alleviation of localized skin paindiscomfort, pruritus, or burning sensation.

Uses

1, Clean your hands and treatment area thoroughly with mild soap and warm water. Dry them afterward.
2, Apply a thick layer of numbing cream to the treatment area, making sure to cover both the tattooed area and its surroundings.
3, Wrap the area securely with plastic wrap and leave it on for 40-60 minutes for the best results (keeping it on longer gives better effects).
4, Remove any remaining cream and wait an additional 5 minutes for the numbing sensation to reach its peak.

Warnings

For external use only.

Stop use and ask a doctor if

rash occurs.

Do not use

if you are allergic to the ingredients in this product or ifthe seal is broken or missing.

When using this product

keep out of eyes. Rinse with water to remove.

Keep out of reach of children.

3. Children under 2 vears: Do not use

If swallowed, get medical help or contact a Poison Control Center right away.

Dosage

Apply to affected area not more than 3 times daily.

Inactive ingredients

Aqua 69%

Mentha Arvensis Leaf Extract, 3%
Zanthoxylum Bungeanum Fruit Extract, 5%
Arnica Montana, 3%
Emu Oil, 2%
Chrysanthellum Indicum Extract, 1%
Propylene Glycol, 5%
Disodium Edta, 1%
Portulaca Oleracea Extract, 1%